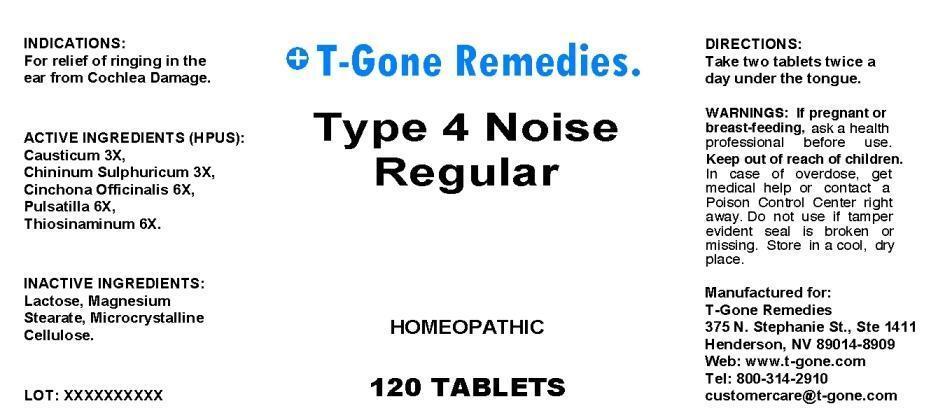 DRUG LABEL: Type 4 Noise Regular
NDC: 50169-0001 | Form: TABLET, ORALLY DISINTEGRATING
Manufacturer: T Gone Remedies
Category: homeopathic | Type: HUMAN OTC DRUG LABEL
Date: 20130402

ACTIVE INGREDIENTS: CAUSTICUM 3 [hp_X]/1 mg; QUININE SULFATE 3 [hp_X]/1 mg; CINCHONA OFFICINALIS BARK 6 [hp_X]/1 mg; PULSATILLA VULGARIS 6 [hp_X]/1 mg; ALLYLTHIOUREA 6 [hp_X]/1 mg
INACTIVE INGREDIENTS: LACTOSE; MAGNESIUM STEARATE; CELLULOSE, MICROCRYSTALLINE

Drug Facts

ACTIVE INGREDIENTS

Causticum 3X, Chininum Sulphuricum 3X, Cinchona Officinalis 6X, Pulsatilla 6X, Thiosinaminum 6X

INDICATIONS

For relief of ringining in the ear from Cochlea Damage.

WARNINGS

If pregnant or breast-feeding, ask a health professional before use. Keep out of reach of children. In case of overdose, get medical help or contact a Poison Control Center right away. Do not use if tamper evident seal is broken or missing. Store in a cool, dry place.

DIRECTIONS

Take two tablets twice a day under the tongue.

INACTIVE INGREDIENTS

Lactose, Magnesium Steareate, Microcrystalline Cellulose

KEEP OUT OF REACH OF CHILDREN

In case of overdose, get medical help or contact a Poison Control Center right away.

INDICATIONS AND USAGE

For relief of ringining in the ear from Cochlea Damage.

QUESTIONS

Manufactured for:

T-Gone Remedies

375 N. Stephanie St., Ste 1411

Henderson, NV 89014-8909

Web: www.t-gone.com

Tel: 800-314-2910

PACKAGE LABEL

T-Gone Remedies

Type 4 Noise Regular

HOMEOPATHIC

120 TABLETS